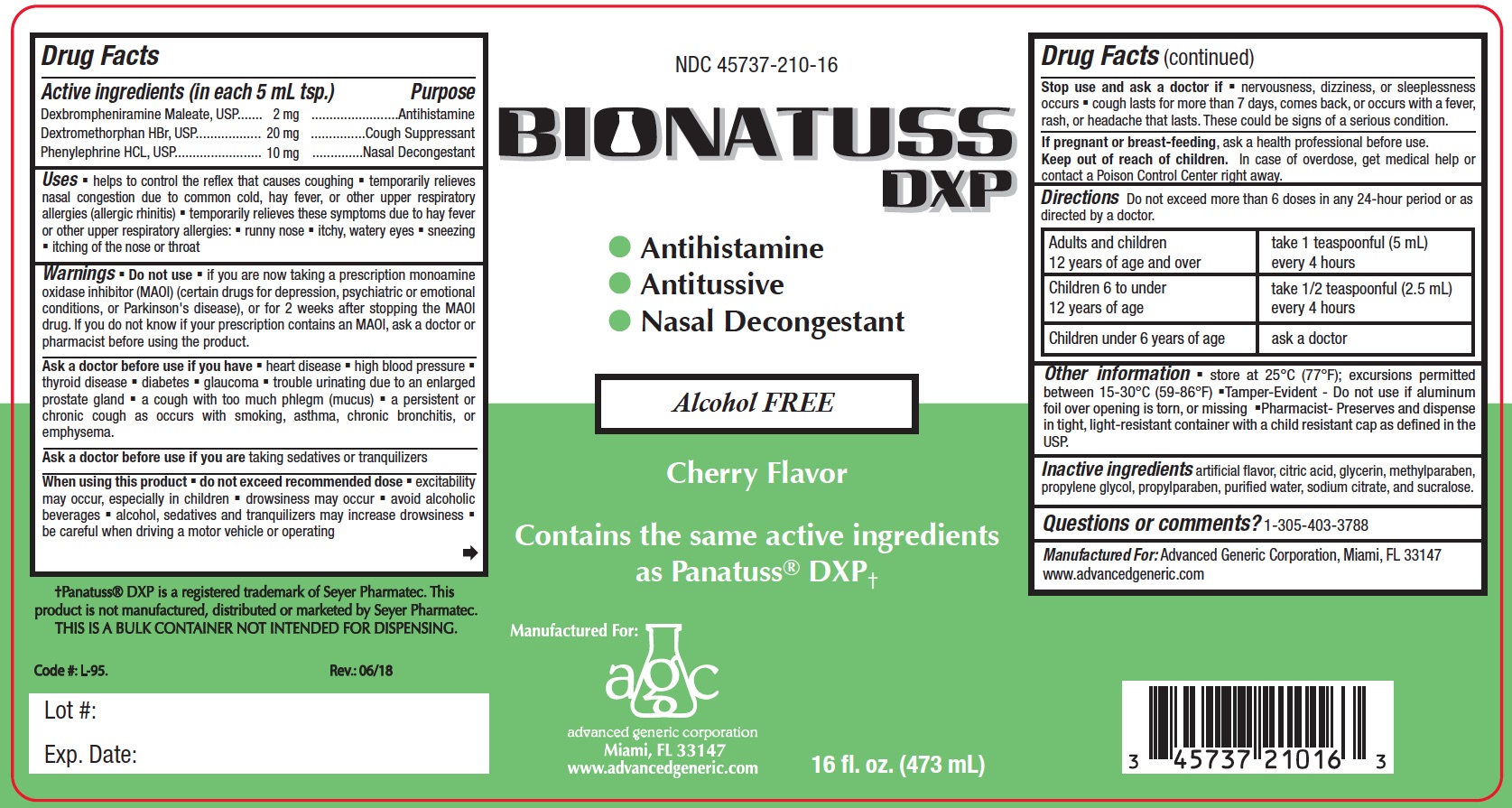 DRUG LABEL: Bionatuss
NDC: 45737-210 | Form: LIQUID
Manufacturer: Advanced Generic Corporation
Category: otc | Type: HUMAN OTC DRUG LABEL
Date: 20241220

ACTIVE INGREDIENTS: DEXBROMPHENIRAMINE MALEATE 2 mg/5 mL; DEXTROMETHORPHAN HYDROBROMIDE 20 mg/5 mL; PHENYLEPHRINE HYDROCHLORIDE 10 mg/5 mL
INACTIVE INGREDIENTS: ANHYDROUS CITRIC ACID; GLYCERIN; METHYLPARABEN; PROPYLENE GLYCOL; PROPYLPARABEN; WATER; SODIUM CITRATE; SUCRALOSE

AGC-BionatussDXP 210

Active Ingredients (in each 5 mL tsp.) Purpose

Dexbrompheniramine Maleate.............2mg................................Antihistamine

Dextromethorphan HBr..................20mg.................................Cough Suppressant

Phenylephrine HCL......................10mg................................. Nasal Descongestant

Purpose

Antihistamine

Cough Suppressant

Nasal Decongestant

Uses

- helps to control the relex that causes coughing
- temporarily relieves nasal congestion due to common cold, hay fever, or other upper respiratory allergies (allergic rhinitis)
- temporarily relieves these symptoms due to hay fever or other upper respiratory allergies:
- runny nose
- itchy, watery eyes
- sneezing
- itching of the nose or throat

Warnings:

Do not use if you are now taking a prescription monoamine oxidase inhibitor (MAOI) (certain drugs for depression, psychiatric or emotional conditions, or Parkinson's disease), or for 2 weeks after stopping the MAOI drug. If you do not know if your prescription contains an MAOI, ask a doctor or pharmacist before using the product.

Ask a doctor before use if you have

- heart disease
- high blood pressure
- thyroid disease
- diabetes
- glaucoma
- trouble urinating due to an enlarged prostate gland
- a cough with too much phlegm (mucus)
- a persistent or chronic cough as occurs with smoking, asthma, chronic bronchitis, or emphysema

Ask a docotor before use if you are taking sedatives or tranquilizers

When using this product

- do not exceed recommended dose
- excitability may occur, especially in children
- drowsiness may occur
- avoid alcoholic beverages
- alcohol, sedatives and tranquilizers may increase drowsiness
- be careful when driving a motor vehicle or operating

Stop use and ask a doctor if

- nervousness, dizziness or sleeplessness occurs
- cough lasts for more than 7 days, comes back, or occurs with a fever, rash, or headache that lasts.
- These could be signs of a serious condition.

Keep out of reach of children.In case of overdose, get medical help or
contact a Poison Control Center right away.

PREGNANCY OR BREAST FEEDING

If pregnant or breast-feeding,ask a health professional before use.

DOSAGE AND ADMINISTRATION

Directions:Do not exceed more than 6 doses in any 24-hour period or
as directed by a doctor.

Adults and children 12 years of age and over | take 1 teaspoonful (5 mL) every 4 hours
Children 6 to under 12 years of age | take 1/2 teaspoonful (2.5 mL) every 4 hours
Children under 6 years of age | ask a doctor

INACTIVE INGREDIENT

Inactive ingredients: artificial flavor, citric acid, glycerin, methylparaben, propylene glycol, propylparaben, water, sodium citrate and sucralose.

Questions or comments?1-305-403-3788